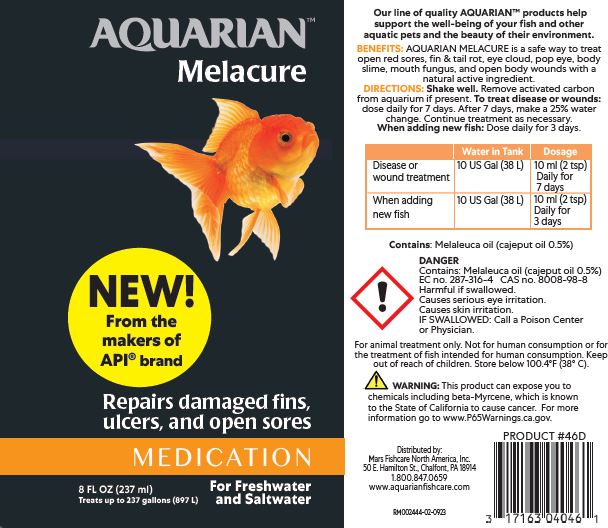 DRUG LABEL: AQUARIAN MELACURE
NDC: 17163-020 | Form: LIQUID
Manufacturer: MARS FISHCARE NORTH AMERICA, INC.
Category: animal | Type: OTC ANIMAL DRUG LABEL
Date: 20240410

ACTIVE INGREDIENTS: CAJUPUT OIL 0.5 g/100 mL

Aquarian Melacure

DESCRIPTION

Our line of quality AQUARIAN products help support the well-being of your fish and other aquatic pets and the beauty of their environment.

INDICATIONS AND USAGE

BENEFITS:

AQUARIAN MELACURE is a safe way to treat open red sores, fin & tail rot, eye cloud, pop eye, body slime, mouth fungus, and open body wounds with a natural active ingredient.

DIRECTIONS:

Shake well.

Remove activated carbon from aquarium if present.

To treat disease or wounds: dose daily for 7 days.

After 7 days, make a 25% water change.

Continue trearment as necessary.

When adding new fish: Dose daily for 3 days.

Water in Tank DOSAGE

Disease or wound treatment 10 US Gal (38L) 10 ml (2 tsp) Daily for 7 days

When adding new fish 10 US Gal (38L) 10 ml (2 tsp) Daily for 3 days

ACTIVE INGREDIENT

Contains: Melaleuca oil (cajeput oil 0.5%)

USER SAFETY WARNINGS

!

DANGER

Contains: Melaleuca oil (cajeput oil 0.5%)

EC no. 287-316-4 CAS no. 8008-98-8

Harmful if swallowed.

Causes serious eye irritation.

Causes skin irritation.

IF SWALLOWED: Call a Poison Center or Physician.

For animal treatment only. Not for human consumption or for treatment of fish intended for human consumption.

Keep out of reach of children. Store below 100.4ºF (38ºC).

!

WARNING: This product can expose you to chemicals including beta-Myrcene, which is known to the State of California to cause cancer. For more information go to www.P65Warnings.ca.gov.